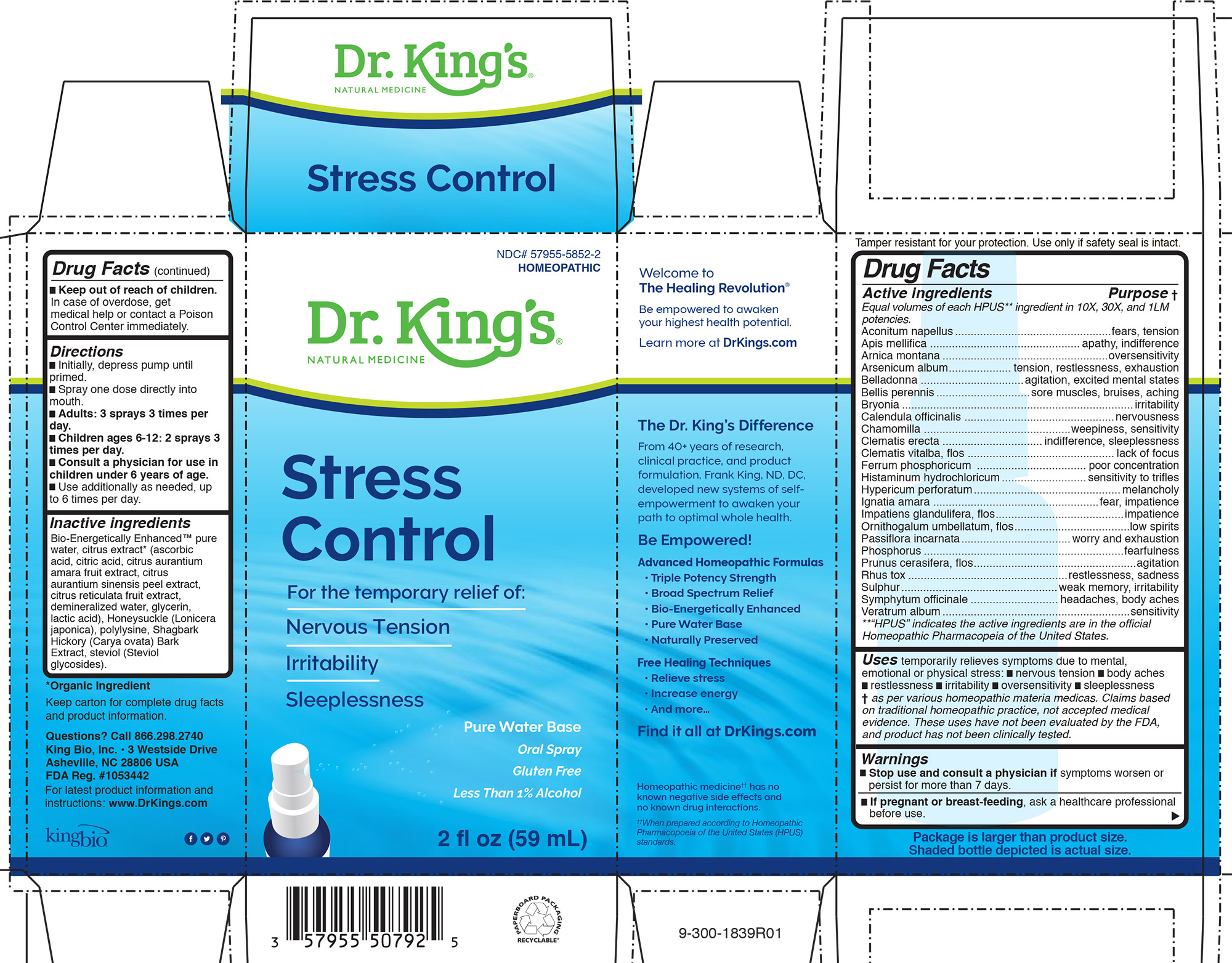 DRUG LABEL: Stress Control
NDC: 57955-5852 | Form: LIQUID
Manufacturer: King Bio Inc.
Category: homeopathic | Type: HUMAN OTC DRUG LABEL
Date: 20210217

ACTIVE INGREDIENTS: ARSENIC TRIOXIDE 10 [hp_X]/59 mL; HISTAMINE DIHYDROCHLORIDE 10 [hp_X]/59 mL; ACONITUM NAPELLUS 10 [hp_X]/59 mL; APIS MELLIFERA 10 [hp_X]/59 mL; ATROPA BELLADONNA 10 [hp_X]/59 mL; BELLIS PERENNIS 10 [hp_X]/59 mL; CLEMATIS VITALBA FLOWER 10 [hp_X]/59 mL; ARNICA MONTANA 10 [hp_X]/59 mL; BRYONIA ALBA ROOT 10 [hp_X]/59 mL; CALENDULA OFFICINALIS FLOWERING TOP 10 [hp_X]/59 mL; MATRICARIA CHAMOMILLA 10 [hp_X]/59 mL; HYPERICUM PERFORATUM 10 [hp_X]/59 mL; CLEMATIS RECTA FLOWERING TOP 10 [hp_X]/59 mL; FERROSOFERRIC PHOSPHATE 10 [hp_X]/59 mL; ORNITHOGALUM UMBELLATUM FLOWERING TOP 10 [hp_X]/59 mL; SULFUR 10 [hp_X]/59 mL; IMPATIENS GLANDULIFERA FLOWER 10 [hp_X]/59 mL; PHOSPHORUS 10 [hp_X]/59 mL; PRUNUS CERASIFERA FLOWER 10 [hp_X]/59 mL; TOXICODENDRON PUBESCENS LEAF 10 [hp_X]/59 mL; STRYCHNOS IGNATII SEED 10 [hp_X]/59 mL; COMFREY ROOT 10 [hp_X]/59 mL; PASSIFLORA INCARNATA FLOWERING TOP 10 [hp_X]/59 mL; VERATRUM ALBUM ROOT 10 [hp_X]/59 mL
INACTIVE INGREDIENTS: POLYEPSILON-LYSINE (4000 MW); LONICERA JAPONICA FLOWER; REBAUDIOSIDE A; WATER; CITRUS BIOFLAVONOIDS; CARYA OVATA BARK

Stress Control

HPUS Active Ingredients

Equal volumes of each HPUS** ingredient in 10X, 30X, and 1LM
potencies.
Aconitum napellus
Apis mellifica
Arnica montana
Arsenicum album
Belladonna
Bellis perennis
Bryonia
Calendula officinalis
Chamomilla
Clematis erecta
Clematis vitalba, flos
Ferrum phosphoricum
Histaminum hydrochloricum
Hypericum perforatum
Ignatia amara
Impatiens glandulifera, flos
Ornithogalum umbellatum, flos
Passiflora incarnata
Phosphorus
Prunus cerasifera, flos
Rhus tox
Sulphur
Symphytum officinale
Veratrum album

Inactive ingredients
Bio-Energetically Enhanced™ pure
water, citrus extract* (ascorbic
acid, citric acid, citrus aurantium
amara fruit extract, citrus
aurantium sinensis peel extract,
citrus reticulata fruit extract,
demineralized water, glycerin,
lactic acid), Honeysuckle (Lonicera
japonica), polylysine, Shagbark
Hickory (Carya ovata) Bark
Extract, steviol (Steviol
glycosides).

INDICATIONS AND USAGE

Uses temporarily relieves symptoms due to mental,
emotional or physical stress: █ nervous tension █ body aches
█ restlessness █ irritability █ oversensitivity █ sleeplessness
† as per various homeopathic materia medicas. Claims based
on traditional homeopathic practice, not accepted medical
evidence. These uses have not been evaluated by the FDA,
and product has not been clinically tested.

Warnings
█ Stop use and consult a physician if symptoms worsen or
persist for more than 7 days.

PREGNANCY OR BREAST FEEDING

█ If pregnant or breast-feeding, ask a healthcare professional
before use.

Keep out of reach of children.

In case of overdose, get medical help or contact a Poison Control Center immediately.

Directions
█ Initially, depress pump until primed.
█ Spray one dose directly into mouth.
█ Adults: 3 sprays 3 times per day.
█ Children ages 6-12: 2 sprays 3 times per day.
█ Consult a physician for use in children under 6 years of age.
█ Use additionally as needed, up to 6 times per day.

PURPOSE

Active ingredients .....................................................Purpose †

Equal volumes of each HPUS** ingredient in 10X, 30X, and 1LM
potencies.

Aconitum napellus..................................................fears, tension
Apis mellifica ................................................apathy, indifference
Arnica montana .....................................................oversensitivity
Arsenicum album.................... tension, restlessness, exhaustion
Belladonna .................................agitation, excited mental states
Bellis perennis..............................sore muscles, bruises, aching
Bryonia ..........................................................................irritability
Calendula officinalis ................................................nervousness
Chamomilla ...............................................weepiness, sensitivity
Clematis erecta ................................indifference, sleeplessness
Clematis vitalba, flos ............................................... lack of focus
Ferrum phosphoricum ................................... poor concentration
Histaminum hydrochloricum...........................sensitivity to trifles
Hypericum perforatum...............................................melancholy
Ignatia amara .....................................................fear, impatience
Impatiens glandulifera, flos.........................................impatience
Ornithogalum umbellatum, flos.....................................low spirits
Passiflora incarnata...................................worry and exhaustion
Phosphorus ................................................................fearfulness
Prunus cerasifera, flos....................................................agitation
Rhus tox ...................................................restlessness, sadness
Sulphur..................................................weak memory, irritability
Symphytum officinale ............................ headaches, body aches
Veratrum album............................................................sensitivity
**“HPUS” indicates the active ingredients are in the official
Homeopathic Pharmacopeia of the United States.

Questions? Call 866.298.2740
King Bio, Inc. • 3 Westside Drive
Asheville, NC 28806 USA
FDA Reg. #1053442

For latest product information and
instructions: www.DrKings.com